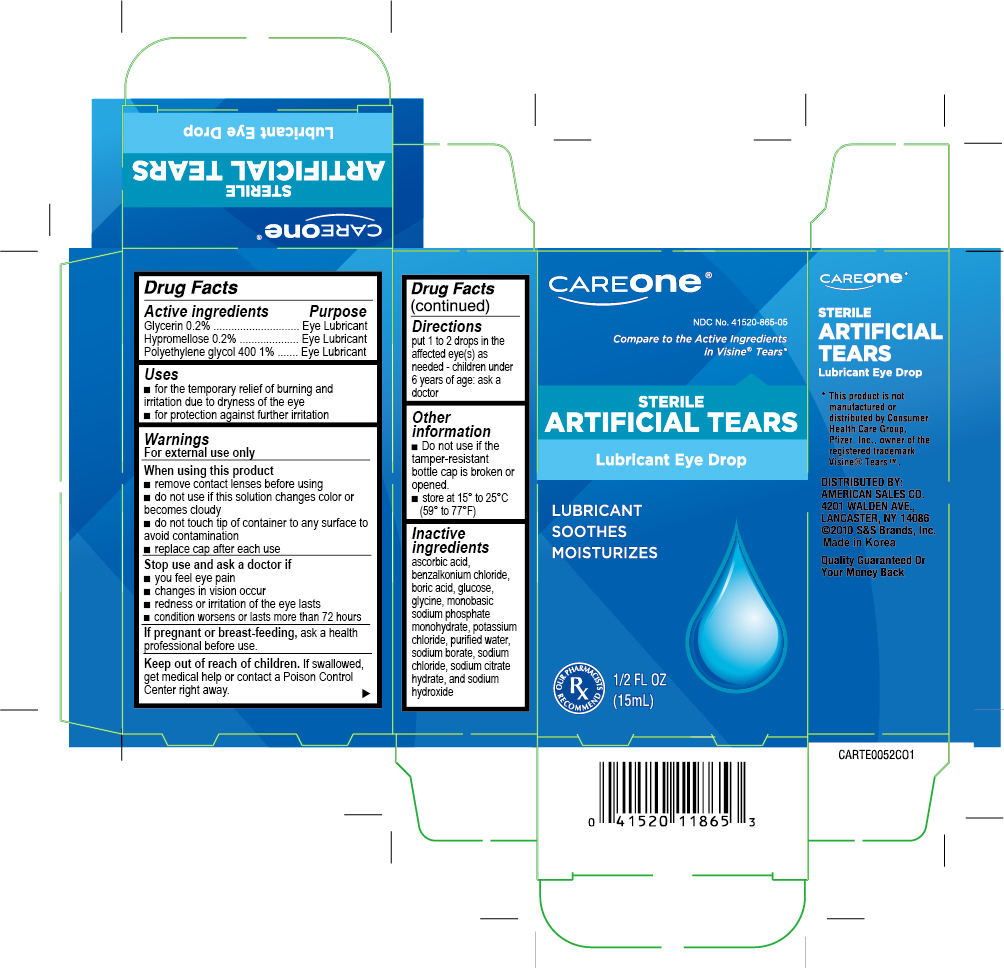 DRUG LABEL: Artificial Tears
NDC: 41520-865 | Form: LIQUID
Manufacturer: American Sales Company
Category: otc | Type: HUMAN OTC DRUG LABEL
Date: 20191028

ACTIVE INGREDIENTS: GLYCERIN 2 mg/1 mL; POLYETHYLENE GLYCOL 400 10 mg/1 mL; HYPROMELLOSES 2 mg/1 mL
INACTIVE INGREDIENTS: ASCORBIC ACID; BENZALKONIUM CHLORIDE; BORIC ACID; DEXTROSE; MAGNESIUM CHLORIDE; POTASSIUM CHLORIDE; WATER; SODIUM BORATE; SODIUM CHLORIDE; SODIUM CITRATE; SODIUM LACTATE; GLYCINE

CareOne Artificial Tears

Active Ingredient

Glycerin 0.2%

Hypromellose 0.2%

Polyethylene Glycol 400 1%

Purpose

Lubricant

Lubricant

Lubricant

Uses

- for use as a protectant against further irritation or to relieve dryness of the eye
- for the temporary relief of discomfort due to minor irritations of the eye, or to exposure to wind or sun

Warnings

Do not use this product if

solution changes color or becomes cloudy

Stop use and ask a doctor if you experience

- eye pain
- changes in vision
- continued redness or irritation of the eye or if the condition worsens or persists for more than 72 hours

When using this product

- to avoid contamination, do not touch tip of container to any surface
- replace cap after using. Keep container tightly closed.
- remove contact lens before using

Keep out of reach of children.

If accidentally swallowed, get medical help or contact a Poison Control Center right away.

Directions

Instill 1 or 2 drops in the affected eye(s) as needed.

Other information

- Do not use if the tamper-resistant bottle cap is broken or opened.
- RETAIN THIS CARTON FOR FUTURE REFERENCE
- store between 15° to 30°C (59°F to 86°F)

Inactive ingredients

aminoacetic acid, ascorbic acid, benzalkonium chloride, boric acid, dextrose, disodium phosphate, magnesium chloride, potassium chloride, purified water, sodium borate, sodium chloride, sodium citrate, sodium lactate

Package principal display panel

Care One Tears